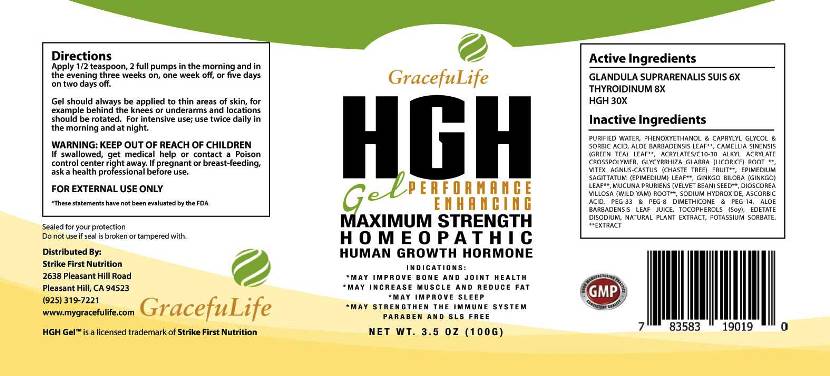 DRUG LABEL: HGH
NDC: 61877-0003 | Form: GEL
Manufacturer: Strike First Nutrition
Category: homeopathic | Type: HUMAN OTC DRUG LABEL
Date: 20160621

ACTIVE INGREDIENTS: SUS SCROFA ADRENAL GLAND 6 [hp_X]/1 g; THYROID, BOVINE 8 [hp_X]/1 g; SOMATROPIN 30 [hp_X]/1 g
INACTIVE INGREDIENTS: PHENOXYETHANOL; CAPRYLYL GLYCOL; SORBIC ACID; ALOE VERA LEAF; GREEN TEA LEAF; CARBOMER INTERPOLYMER TYPE A (ALLYL SUCROSE CROSSLINKED); GLYCYRRHIZA GLABRA; CHASTE TREE; EPIMEDIUM SAGITTATUM TOP; GINKGO; MUCUNA PRURIENS SEED; DIOSCOREA VILLOSA ROOT; SODIUM HYDROXIDE; ASCORBIC ACID; POLYETHYLENE GLYCOL 1500; PEG-8 DIMETHICONE; POLYETHYLENE GLYCOL 700; TOCOPHEROL; EDETATE DISODIUM; OREGANO; POTASSIUM SORBATE

Drug Facts:

ACTIVE INGREDIENTS:

Glandula Suprarenalis Suis 6X, Thyroidinum (Bovine) 8X, HGH 30X

INDICATIONS

- May improve bone and joint health
- May increase muscle and reduce fat
- May improve sleep
- May strengthen the immune system

*These statements have not been evaluated by the FDA

WARNINGS:

KEEP OUT OF REACH OF CHILDREN. If swallowed, get medical help or contact a Poison control center right away.

If pregnant or breast-feeding, ask a health professional before use.

FOR EXTERNAL USE ONLY

KEEP OUT OF REACH OF CHILDREN. If swallowed, get medical help or contact a Poison control center right away.

DIRECTIONS:

Apply 1/2 teaspoon, 2 full pumps in the morning and in the evening three weeks on, one week off, or five days on two days off.

Gel should always be applied to thin areas of skin, for example behind the knees or underarms and locations should be rotated. For intensive use; use twice daily in the morning and at night.

INDICATIONS:

- May improve bone and joint health
- May increase muscle and reduce fat
- May improve sleep
- May strengthen the immune system

*These statements have not been evaluated by the FDA

INACTIVE INGREDIENTS:

Phenoxyethanol, Caprylyl Glycol, Sorbic Acid, Aloe Vera (Leaf), Green Tea (Leaf), Acrylates/C10-30 Alkyl Acrylate Crosspolymer, Licorice (Root), Chaste Tree (Fruit), Epimedium (Aerial Parts), Ginkgo (Leaf), Velvet Bean (Seed), Wild Yam (Root), Sodium Hydroxide, Ascorbic Acid (Vitamin C), PEG-33, PEG-8 Dimethicone, PEG-14, Aloe Barbadensis Leaf, Tocopherol (Vitamin E Oil From Soybean), Edetate Disodium, Oregano, Potassium Sorbate

QUESTIONS:

Distributed By:

Strike First Nutrition

2638 Pleasant Hill Road

Pleasant Hill, CA 94523

(925) 319-7221

www.mygracefullife.com

PACKAGE LABEL DISPLAY:

GracefulLife

HGH

Gel

PERFORMANCE ENHANCING

MAXIMUM STRENGTH

HOMEOPATHIC

HUMAN GROWTH HORMONE

May improve bone and joint health
May increase muscle and reduce fat
May improve sleep
May strengthen the immune system

PARABEN AND SLS FREE

NET WT. 3.5 OZ (100G)